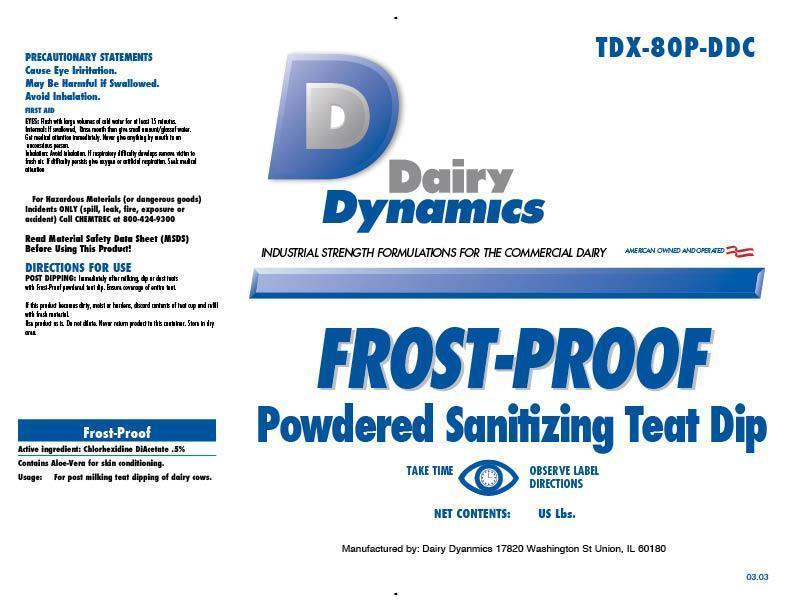 DRUG LABEL: FROST-PROOF
NDC: 67351-980 | Form: POWDER
Manufacturer: Dairy Dynamics L.L.C.
Category: animal | Type: OTC ANIMAL DRUG LABEL
Date: 20150113

ACTIVE INGREDIENTS: CHLORHEXIDINE DIACETATE .005 kg/1 kg
INACTIVE INGREDIENTS: DIDECYLDIMONIUM CHLORIDE; ALUMINUM SILICATE; AMMONIUM CHLORIDE; ALOE VERA LEAF

Dairy Dynamics
FROST-PROOF
Powdered Sanitizing Teat Dip

WARNINGS AND PRECAUTIONS

Dairy Dynamics

INDUSTRIAL STRENGTH FORMULATIONS FOR THE COMMERCIAL DAIRY

AMERICAN OWNED AND OPERATED

WARNINGS AND PRECAUTIONS

PRECAUTIONARY STATEMENTS

Cause Eye Irritation.

May Be Harmful if Swallowed.

Avoid Inhalation.

FIRST AID

EYES: Flush with large volumes of cold water for at least 15 minutes.

Internal: If swallowed, Rinse mouth then give small amount/glass of water.

Get medical attention immediately. Never give anything by mouth to an unconscious person.

Inhalation: Avoid inhalation. If respiratory difficulty develops remove victim to fresh air. If difficulty persists give oxygen or artificial respiration.

Seek medical attention.

For Hazardous Materials (or dangerous goods) Incidents ONLY (spill, leak, fire, exposure or accident) Call CHEMTREC at 800-424-9300

Read Material Safety Data Sheet (MSDS) Before Using This Product!

DIRECTIONS FOR USE

POST DIPPING: Immediately after milking, dip or dust teats with Frost-Proof powdered teat dip. Ensure coverage of entire teat.

If this product becomes dirty, moist or hardens, discard contents of teat cup and refill with fresh material.

Use product as is. Do not dilute. Never return product to this container.

Store in dry area.

ACTIVE INGREDIENT

Frost-Proof

Active ingredient: Chlorhexidene DiAcetate .5%

INACTIVE INGREDIENT

Contains Aloe-Vera for skin conditining.

PURPOSE

Usage: For post milking teat dipping dairy cows.

TAKE TIME OBSERVE LABEL DIRECTIONS

NET CONTENTS: 15 US Lbs

Manufactured by: Dairy Dynamics 17820 Washington St Union, IL 60180

TDX-80P-DDC

LOT:

Exp:

03.03